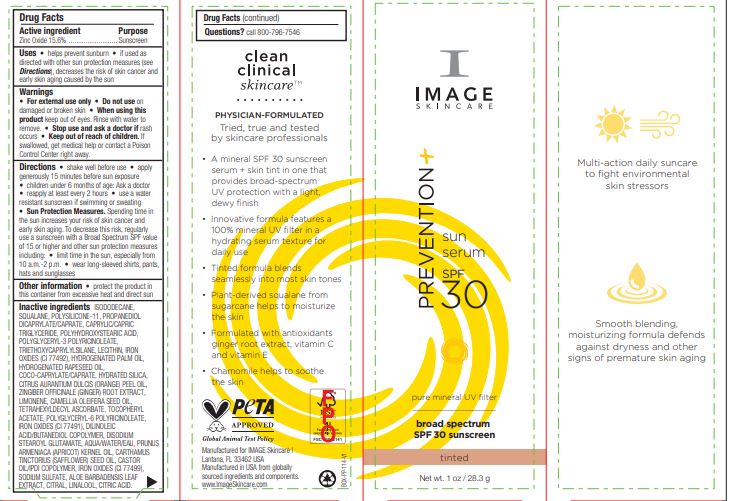 DRUG LABEL: Prevention Sun Serum SPF 30 Tinted
NDC: 62742-4224 | Form: CREAM
Manufacturer: Allure Labs
Category: otc | Type: HUMAN OTC DRUG LABEL
Date: 20241209

ACTIVE INGREDIENTS: ZINC OXIDE 15.6 g/100 g
INACTIVE INGREDIENTS: ISODODECANE; HYDROGENATED RAPESEED OIL; LIMONENE, (+)-; CAMELLIA OIL; SAFFLOWER OIL; COCO-CAPRYLATE/CAPRATE; LECITHIN, SOYBEAN; MEDIUM-CHAIN TRIGLYCERIDES; POLYGLYCERYL-6 POLYRICINOLEATE; WATER; PROPANEDIOL DICAPRYLATE/CAPRATE; POLYGLYCERYL-3 PENTARICINOLEATE; CITRIC ACID MONOHYDRATE; FERROSOFERRIC OXIDE; ALOE VERA LEAF; CITRAL; ORANGE OIL; APRICOT KERNEL OIL; SQUALANE; DIMETHICONE/VINYL DIMETHICONE CROSSPOLYMER (SOFT PARTICLE); POLYHYDROXYSTEARIC ACID (2300 MW); TRIETHOXYCAPRYLYLSILANE; .ALPHA.-TOCOPHEROL ACETATE; FERRIC OXIDE RED; DISODIUM STEAROYL GLUTAMATE; CASTOR OIL; LINALOOL, (+/-)-; HYDRATED SILICA; GINGER; FERRIC OXIDE YELLOW; HYDROGENATED PALM OIL; TETRAHEXYLDECYL ASCORBATE; DILINOLEIC ACID/BUTANEDIOL COPOLYMER; SODIUM SULFATE

Drug Facts

Active ingredient

Zinc Oxide 15.6%

Purpose

Sunscreen

Uses

Helps prevent sunburn • if used as directed with other sun protection measures (see Directions), decreases the risk of skin cancer and early skin aging caused by the sun

Warnings

For external use only

Do not use on damaged or broken skin

When using this product keep out of eyes. Rinse with water to remove

Stop use and ask a doctor if rash occurs

Keep out of reach of children. If swallowed, get medical help or contact a Poison Control Center right away

DOSAGE AND ADMINISTRATION

Directions • shake well before use • apply generously 15 minutes before sun exposure • children under 6 months of age: Ask a doctor • reapply at least every 2 hours • use a water resistant sunscreen if swimming or sweating • Sun Protection Measures. Spending time in the sun increases your risk of skin cancer and early skin aging. To decrease this risk, regularly use a sunscreen with a Broad Spectrum SPF value of 15 or higher and other sun protection measures including: • limit time in the sun, especially from 10 a.m.-2 p.m. • wear long-sleeved shirts, pants, hats and sunglasses

Other information • protect the product in this container from excessive heat and direct sun

Inactive ingredients

ISODODECANE, SQUALANE, POLYSILICONE-11, PROPANEDIOL DICAPRYLATE/CAPRATE, CAPRYLIC/CAPRIC TRIGLYCERIDE, POLYHYDROXYSTEARIC ACID, POLYGLYCERYL-3 POLYRICINOLEATE, TRIETHOXYCAPRYLYLSILANE, LECITHIN, IRON OXIDES (CI 77492), HYDROGENATED PALM OIL, HYDROGENATED RAPESEED OIL, COCO-CAPRYLATE/CAPRATE, HYDRATED SILICA, CITRUS AURANTIUM DULCIS (ORANGE) PEEL OIL, ZINGIBER OFFICINALE (GINGER) ROOT EXTRACT, LIMONENE, CAMELLIA OLEIFERA SEED OIL, TETRAHEXYLDECYL ASCORBATE, TOCOPHERYL ACETATE, POLYGLYCERYL-6 POLYRICINOLEATE, IRON OXIDES (CI 77491), DILINOLEIC ACID/BUTANEDIOL COPOLYMER, DISODIUM STEAROYL GLUTAMATE, AQUA/WATER/EAU, PRUNUS ARMENIACA (APRICOT) KERNEL OIL, CARTHAMUS TINCTORIUS (SAFFLOWER) SEED OIL, CASTOR OIL/IPDI COPOLYMER, IRON OXIDES (CI 77499), SODIUM SULFATE, ALOE BARBADENSIS LEAF EXTRACT, CITRAL, LINALOOL, CITRIC ACID.